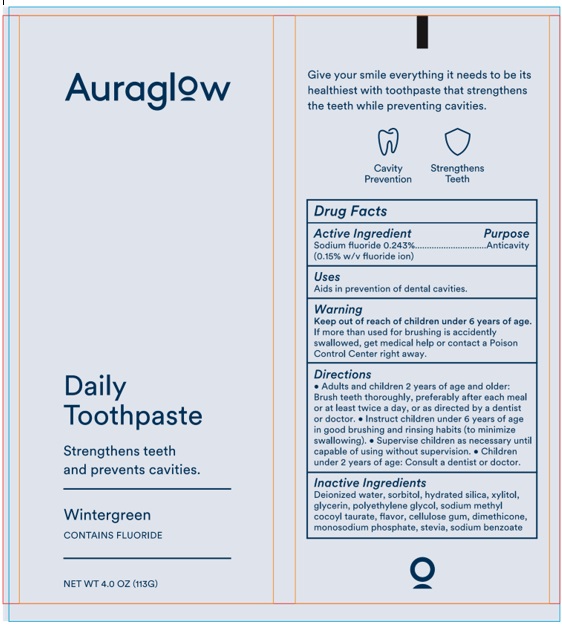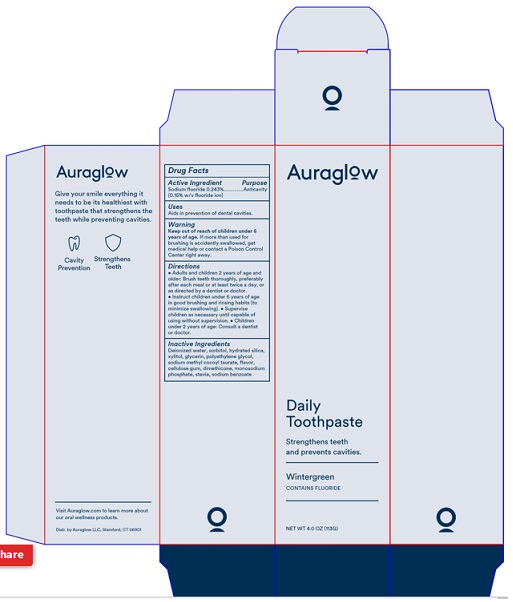 DRUG LABEL: Auraglow Daily
NDC: 81740-002 | Form: PASTE, DENTIFRICE
Manufacturer: Auraglow LLC
Category: otc | Type: HUMAN OTC DRUG LABEL
Date: 20221107

ACTIVE INGREDIENTS: SODIUM FLUORIDE 2.43 mg/1 g
INACTIVE INGREDIENTS: WATER; SORBITOL; HYDRATED SILICA; XYLITOL; GLYCERIN; POLYETHYLENE GLYCOL 1600; SODIUM METHYL COCOYL TAURATE; CARBOXYMETHYLCELLULOSE SODIUM, UNSPECIFIED; DIMETHICONE; SODIUM PHOSPHATE, MONOBASIC, UNSPECIFIED FORM; STEVIA REBAUDIUNA LEAF; SODIUM BENZOATE

Auraglow Daily Toothpaste

Drug Facts

Active ingredient

Sodium fluoride 0.243%

(0.15% w/v fluoride ion)

Purpose Anticavity

INDICATIONS AND USAGE

Use Aids in prevention of dental cavities.

Warnings

Keep out of reach of children under 6 years of age.

If more than used for brushing is accidentally swallowed, get

medical help or contact a Poison Control Center right away.

Directions

• Adults and children 2 years of age and older:
Brush teeth thouroughly, preferably after each meal or
at least twice a day, or as directed by a dentist or doctor.
• Instruct children under 6 years of age in good brushing
and rinsing habits (to minimize swallowing). • Supervise
children as necessary until capable of using without supervision.

• Children under 2 years of age: Consult a dentist or doctor.

Inactive Ingredients

Deionized water, sorbitol, hydrated silica, xylitol,

glycerin, polyethylene glycol, sodium methyl

cocoyl taurate, flavor, cellulose gum, dimethicone,

monosodium phosphate, stevia, sodium benzoate

Package Labeling

Auraglow

Daily

Toothpaste

Strengthens Teeth

and prevents cavities.

_____________________

Wintergreen

CONTAINS FLUORIDE

_____________________

NET WT 4.0 OZ (113G)

Distr. by Auraglow LLC, Stamford, CT 06901

res